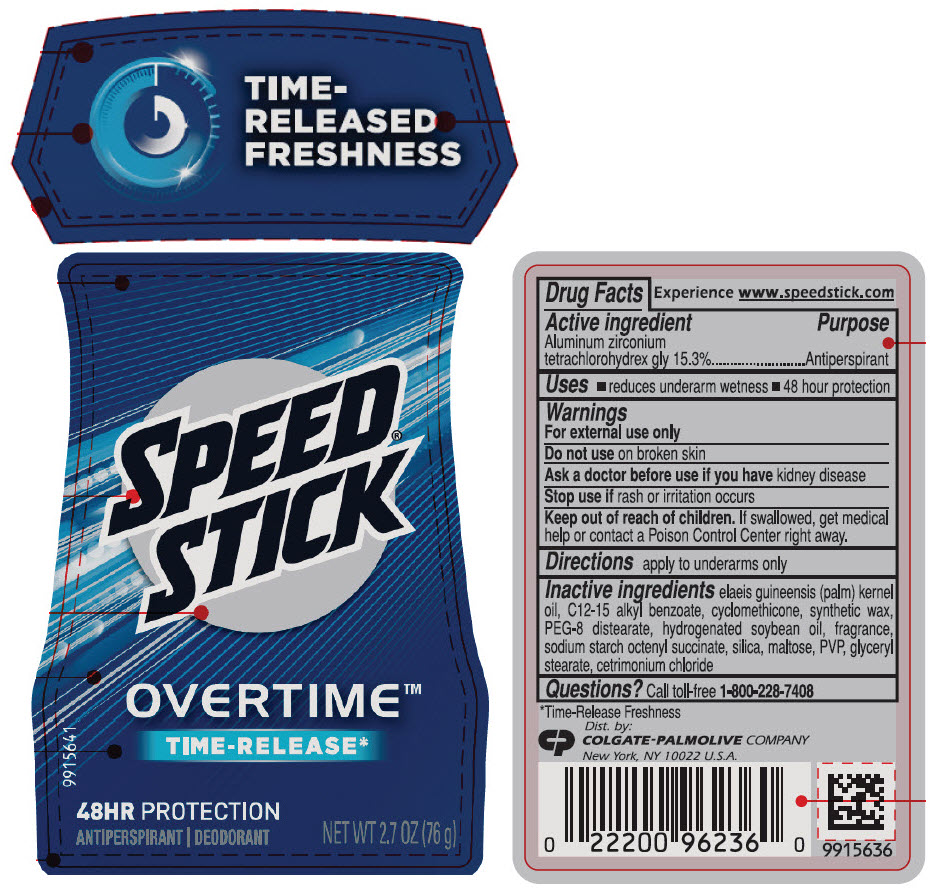 DRUG LABEL: Speed Stick Gear Overtime Relentless Antiperspirant Deodorant
NDC: 35000-729 | Form: STICK
Manufacturer: COLGATE PALMOLIVE COMPANY
Category: otc | Type: HUMAN OTC DRUG LABEL
Date: 20191216

ACTIVE INGREDIENTS: ALUMINUM ZIRCONIUM TETRACHLOROHYDREX GLY 153 mg/1 g
INACTIVE INGREDIENTS: PALM KERNEL OIL; ALKYL (C12-15) BENZOATE; CYCLOMETHICONE; PARAFFIN; PEG-8 DISTEARATE; HYDROGENATED SOYBEAN OIL; SILICON DIOXIDE; MALTOSE, UNSPECIFIED FORM; POVIDONE, UNSPECIFIED; GLYCERYL MONOSTEARATE; CETRIMONIUM CHLORIDE

Speed Stick® Gear™ Overtime™ Relentless™ Antiperspirant Deodorant (2.7oz)

Drug Facts

Active ingredient

Aluminum zirconium tetrachlorohydrex gly 15.3%

Purpose

Antiperspirant

Uses

- reduces underarm wetness
- 48 hour protection

Warnings

For external use only

Do not use on broken skin

Ask a doctor before use if you have kidney disease

Stop use if rash or irritation occurs

Keep out of reach of children. If swallowed, get medical help or contact a Poison Control Center right away.

Directions

apply to underarms only

Inactive ingredients

elaeis guineensis (palm) kernel oil, C12-15 alkyl benzoate, cyclomethicone, synthetic wax, PEG-8 distearate, hydrogenated soybean oil, fragrance, sodium starch octenyl succinate, silica, maltose, PVP, glyceryl stearate, cetrimonium chloride

Questions?

Call toll-free 1-800-228-7408

Dist. by:
COLGATE-PALMOLIVE COMPANY
New York, NY 10022

PRINCIPAL DISPLAY PANEL - 76 g Container Label

TIME-
RELEASED
FRESHNESS

SPEED®
STICK

OVERTIME™

TIME-RELEASE*

48HR PROTECTION
ANTIPERSPIRANT | DEODORANT

NET WT 2.7 OZ (76 g)

9915641